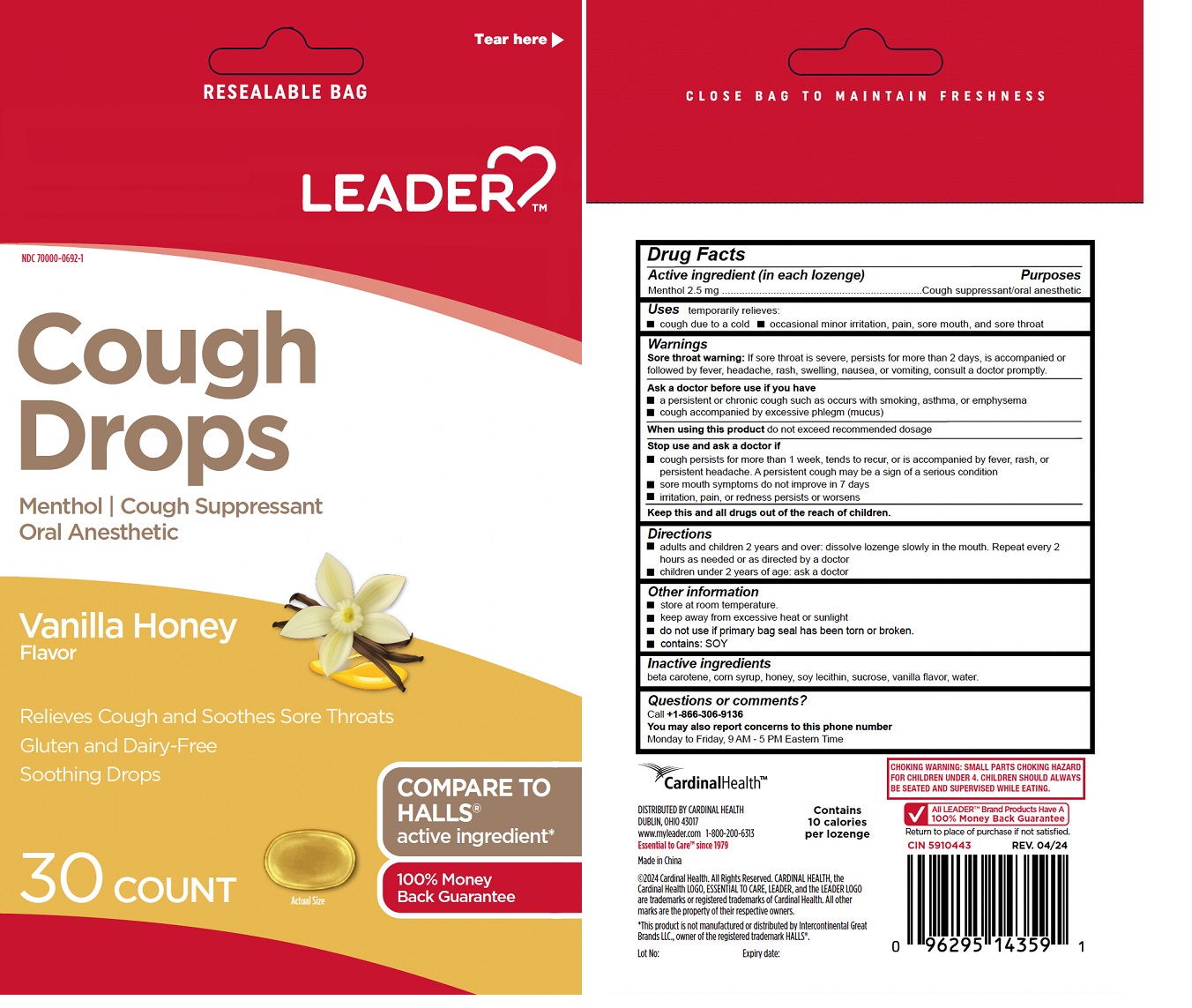 DRUG LABEL: Leader Cough Drops Vanilla Honey
NDC: 83698-692 | Form: LOZENGE
Manufacturer: Xiamen Kang Zhongyuan Biotechnology Co., Ltd.
Category: otc | Type: HUMAN OTC DRUG LABEL
Date: 20251226

ACTIVE INGREDIENTS: MENTHOL, UNSPECIFIED FORM 2.5 mg/1 1
INACTIVE INGREDIENTS: BETA CAROTENE; CORN SYRUP; HONEY; SOYBEAN LECITHIN; SUCROSE; WATER

LEADERTMCough Drops Vanilla Honey Flavor

Active ingredient (in each lozenge)

Menthol 2.5 mg

Purposes

Cough suppressant/oral anesthetic

Uses

temporarily relieves:
• cough due to a cold • occasional minor irritation, pain, sore mouth, and sore throat

Warnings

Sore throat warning:If sore throat is severe, persists for more than 2 days, is accompanied or followed by fever, headache, rash, swelling, nausea, or vomiting, consult a doctor promptly.

Ask a doctor before use if you have
• a persistent or chronic cough such as occurs with smoking, asthma, or emphysema
• cough accompanied by excessive phlegm (mucus)

When using this productdo not exceed recommended dosage

Stop use and ask a doctor if
• cough persists for more than 1 week, tends to recur, or is accompanied by fever, rash, or persistent headache. A persistent cough may be a sign of a serious condition
• sore mouth symptoms do not improve in 7 days
• irritation, pain, or redness persists or worsens

KEEP OUT OF REACH OF CHILDREN

Keep this and all drugs out of the reach of children.

Directions

• adults and children 2 years and over: dissolve lozenge slowly in the mouth. Repeat every 2 hours as needed or as directed by a doctor
• children under 2 years of age: ask a doctor

Other information

• store at room temperature.
• keep away from excessive heat or sunlight
• do not use if primary bag seal has been torn or broken.
• contains: SOY

Inactive ingredients

beta carotene, corn syrup, honey, soy lecithin, sucrose, vanilla flavor, water.

Questions or comments?

Call +1-866-306-9136
You may also report concerns to this phone number
Monday to Friday, 9 AM -5 PM Eastern Time

RESEALABLE BAG

Gluten and Dairy-Free

Soothing Drops

COMPARE TO HALLS® active ingredient*

CLOSE BAG TO MAINTAIN FRESHNESS

CardinalHealth™

DISTRIBUTED BY CARDINAL HEALTH
DUBLIN, OHIO 43017
www.myleader.com 1-800-200-6313
Essential to Care™ Since 1979

Made in China

©2024 Cardinal Health. All Rights Reserved. CARDINAL HEALTH, the Cardinal Health LOGO, ESSENTIAL TO CARE, LEADER, and the LEADER LOGO are trademarks or registered trademarks of Cardinal Health. All other marks are the property of their respective owners.

*This product is not manufactured or distributed by Intercontinental Great Brands LLC., owner of the registered trademark HALLS®.

Contains 10 calories per lozenge

CHOKING WARNING: SMALL PARTS CHOKING HAZARD FOR CHILDREN UNDER 4. CHILDREN SHOULD ALWAYS BE SEATED AND SUPERVISED WHILE EATING.

All LEADER™ Brand Products Have A 100% Money Back Guarantee
Return to place of purchase if not satisfied.